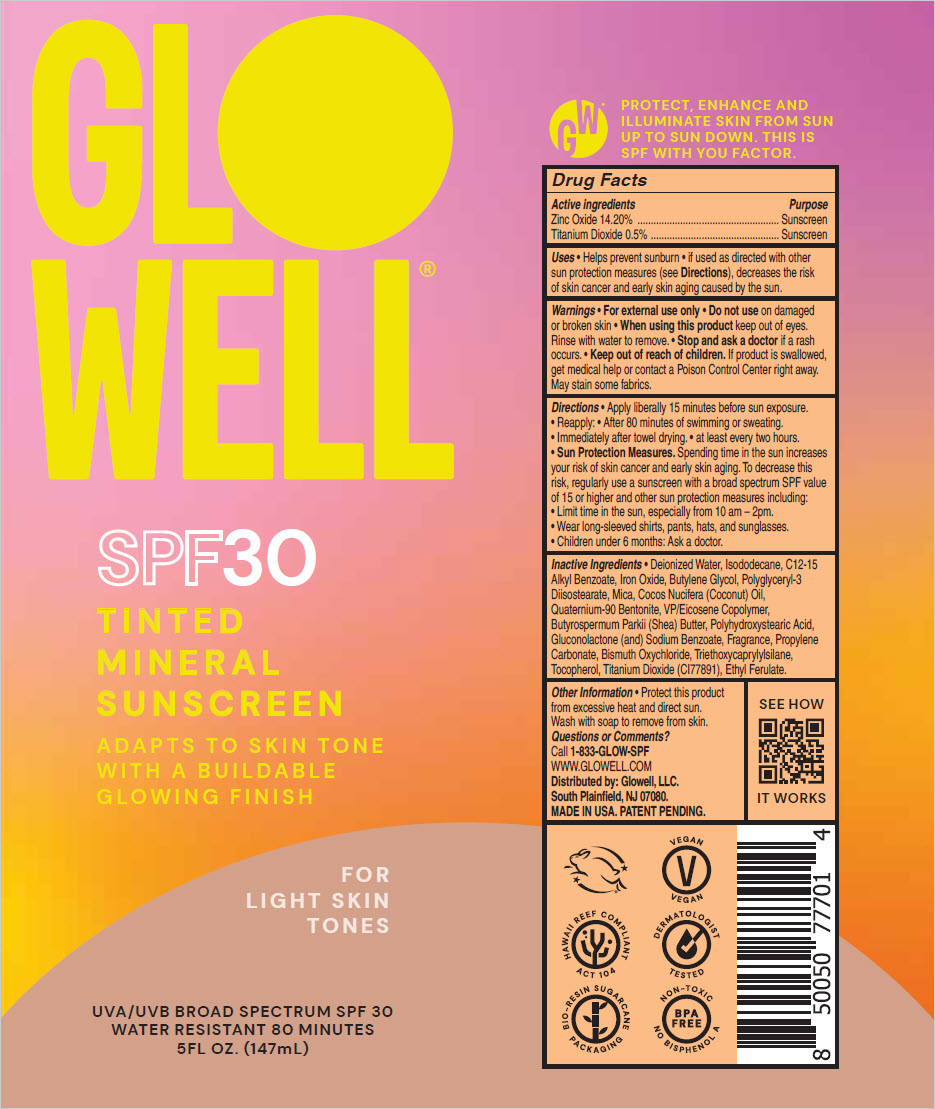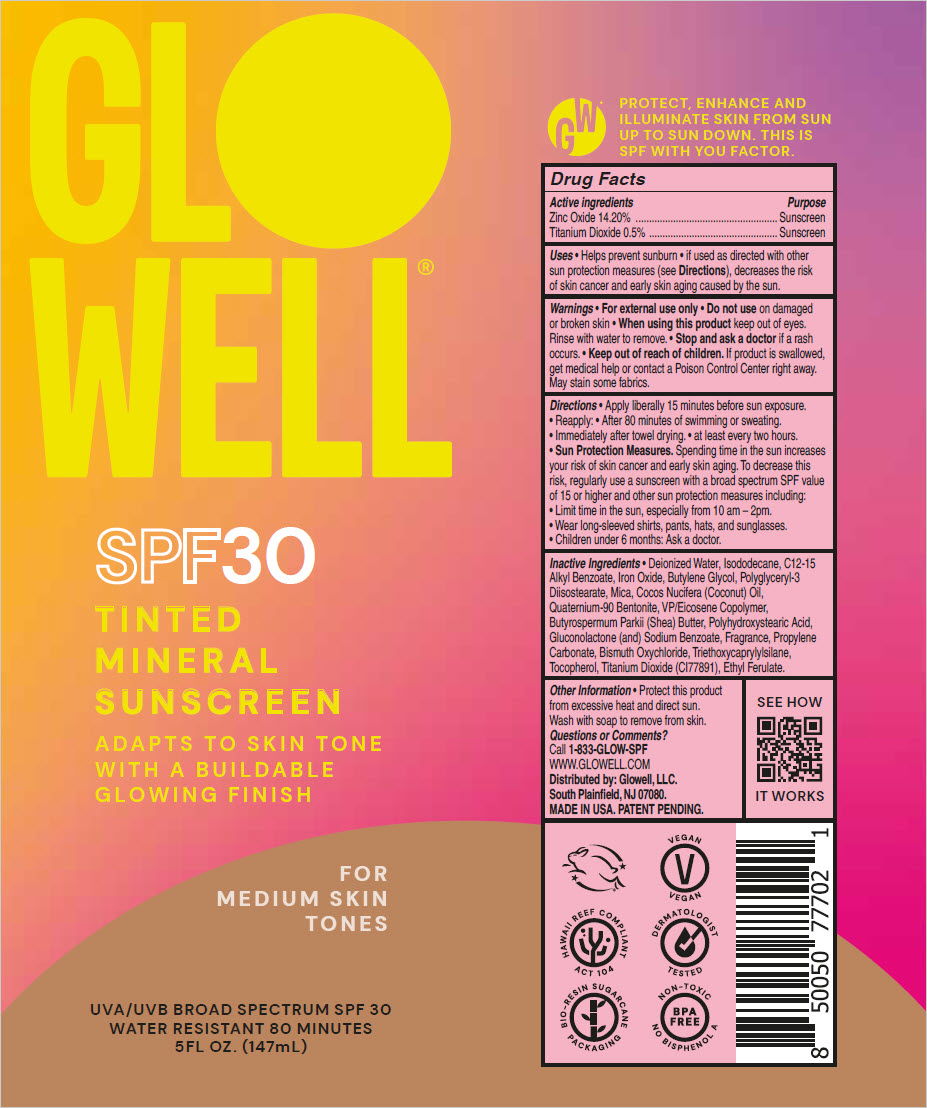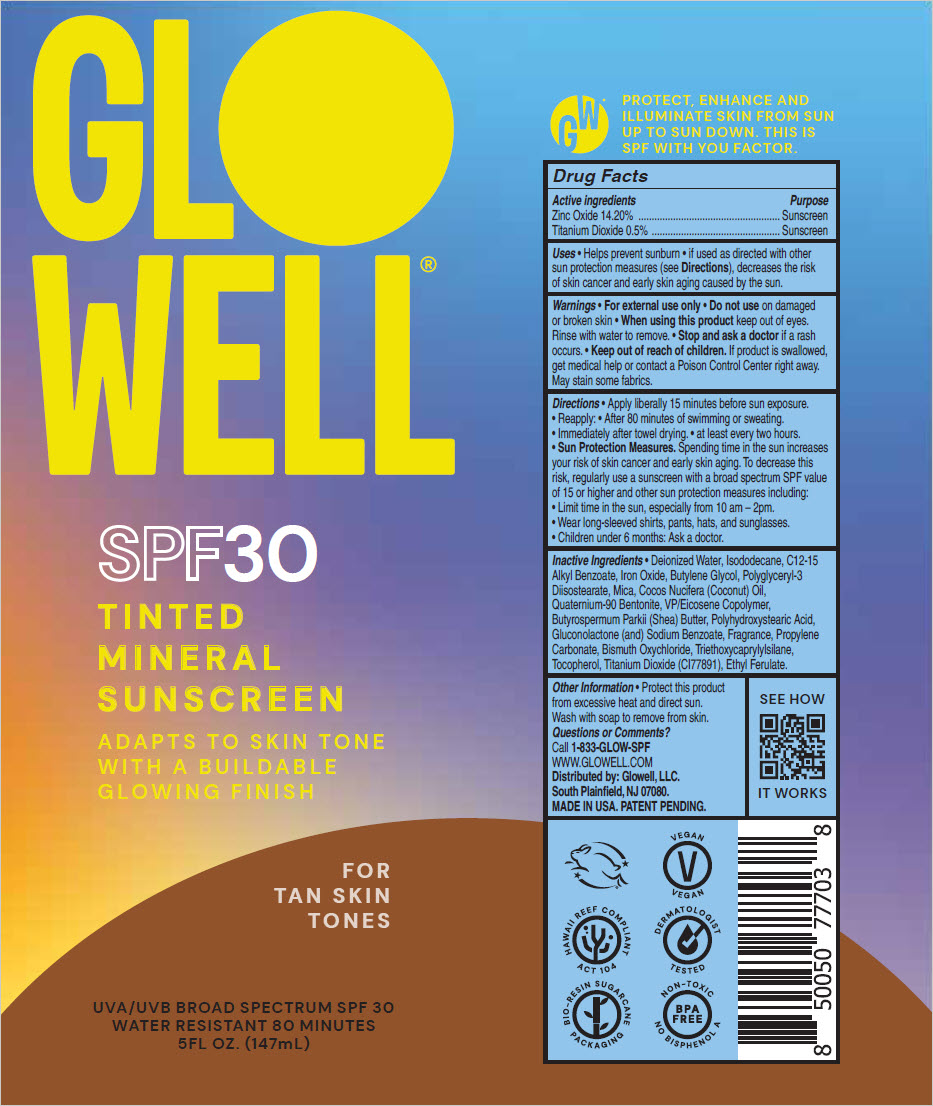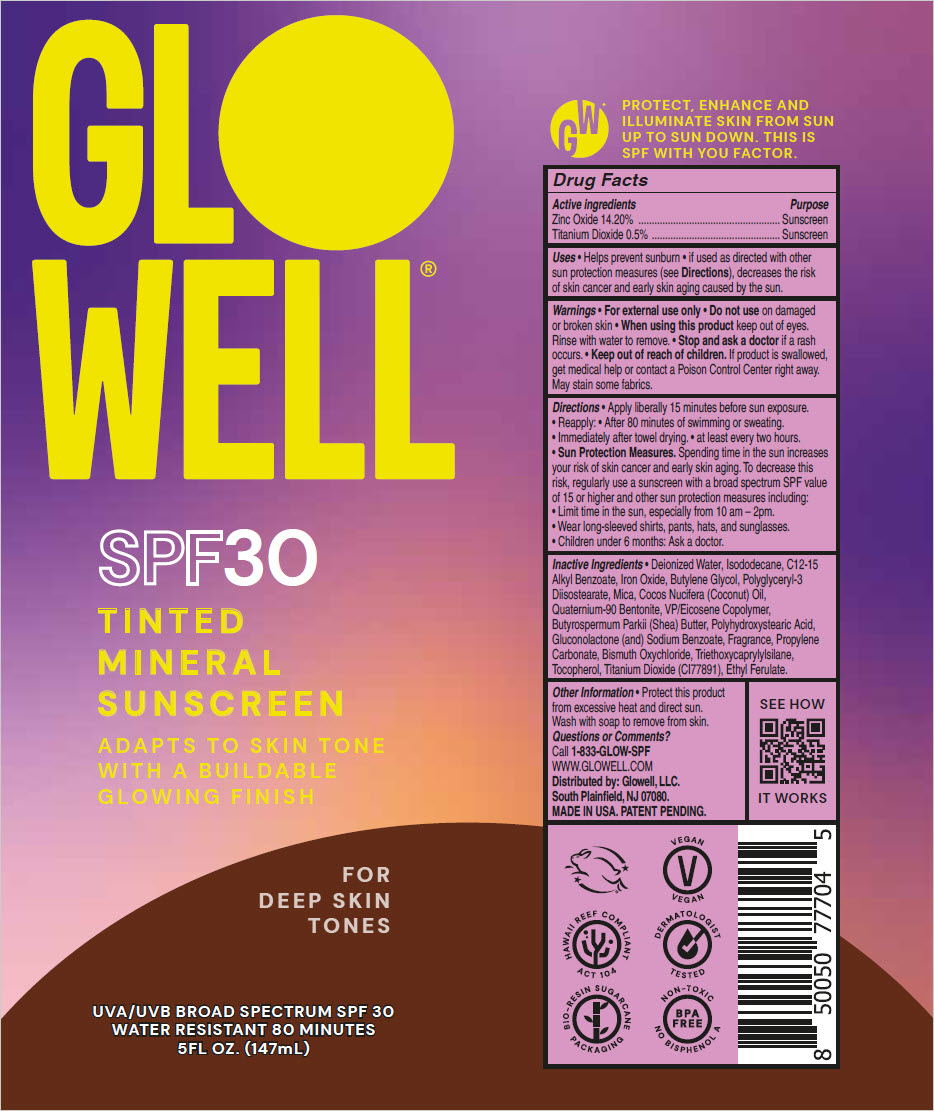 DRUG LABEL: Glowell SPF 30 Tinted Mineral Sunscreen 
NDC: 83495-101 | Form: CREAM
Manufacturer: GLOWELL, LLC.
Category: otc | Type: HUMAN OTC DRUG LABEL
Date: 20230620

ACTIVE INGREDIENTS: ZINC OXIDE 0.142 g/1 mL; TITANIUM DIOXIDE 0.005 g/1 mL
INACTIVE INGREDIENTS: WATER; ISODODECANE; ALKYL (C12-15) BENZOATE; FERRIC OXIDE RED; BUTYLENE GLYCOL; POLYGLYCERYL-3 DIISOSTEARATE; MICA; COCONUT OIL; QUATERNIUM-90 BENTONITE; VINYLPYRROLIDONE/EICOSENE COPOLYMER; SHEA BUTTER; GLUCONOLACTONE; SODIUM BENZOATE; PROPYLENE CARBONATE; BISMUTH OXYCHLORIDE; TRIETHOXYCAPRYLYLSILANE; TOCOPHEROL; ETHYL FERULATE

Glowell® SPF 30 Tinted Mineral Sunscreen

Drug Facts

ACTIVE INGREDIENT

Active ingredients | Purpose
Zinc Oxide 14.20% | Sunscreen
Titanium Dioxide 0.5% | Sunscreen

Uses

- Helps prevent sunburn
- if used as directed with other sun protection measures (see Directions), decreases the risk of skin cancer and early skin aging caused by the sun.

Warnings

- For external use only
- Do not use on damaged or broken skin
- When using this product keep out of eyes. Rinse with water to remove.
- Stop and ask a doctor if a rash occurs.

- Keep out of reach of children. If product is swallowed, get medical help or contact a Poison Control Center right away. May stain some fabrics.

Directions

- Apply liberally 15 minutes before sun exposure.
- Reapply:
  - After 80 minutes of swimming or sweating.
  - Immediately after towel drying.
  - at least every two hours.
- Sun Protection Measures. Spending time in the sun increases your risk of skin cancer and early skin aging. To decrease this risk, regularly use a sunscreen with a broad spectrum SPF value of 15 or higher and other sun protection measures including:
  - Limit time in the sun, especially from 10 am – 2pm.
  - Wear long-sleeved shirts, pants, hats, and sunglasses.
- Children under 6 months: Ask a doctor.

Inactive Ingredients

- Deionized Water, Isododecane, C12-15 Alkyl Benzoate, Iron Oxide, Butylene Glycol, Polyglyceryl-3 Diisostearate, Mica, Cocos Nucifera (Coconut) Oil, Quaternium-90 Bentonite, VP/Eicosene Copolymer, Butyrospermum Parkii (Shea) Butter, Polyhydroxystearic Acid, Gluconolactone (and) Sodium Benzoate, Fragrance, Propylene Carbonate, Bismuth Oxychloride, Triethoxycaprylylsilane, Tocopherol, Titanium Dioxide (CI77891), Ethyl Ferulate.

Other Information

- Protect this product from excessive heat and direct sun. Wash with soap to remove from skin.

Questions or Comments?

Call 1-833-GLOW-SPF

Distributed by: Glowell, LLC.
South Plainfield, NJ 07080.

PRINCIPAL DISPLAY PANEL - 147 mL Tube Label - Light

GLO
WELL®

SPF30

TINTED
MINERAL
SUNSCREEN

ADAPTS TO SKIN TONE
WITH A BUILDABLE
GLOWING FINISH

FOR
LIGHT SKIN
TONES

UVA/UVB BROAD SPECTRUM SPF 30
WATER RESISTANT 80 MINUTES
5FL OZ. (147mL)

PRINCIPAL DISPLAY PANEL - 147 mL Tube Label - Medium

GLO
WELL®

SPF30

TINTED
MINERAL
SUNSCREEN

ADAPTS TO SKIN TONE
WITH A BUILDABLE
GLOWING FINISH

FOR
MEDIUM SKIN
TONES

UVA/UVB BROAD SPECTRUM SPF 30
WATER RESISTANT 80 MINUTES
5FL OZ. (147mL)

PRINCIPAL DISPLAY PANEL - 147 mL Tube Label - Tan

GLO
WELL®

SPF30

TINTED
MINERAL
SUNSCREEN

ADAPTS TO SKIN TONE
WITH A BUILDABLE
GLOWING FINISH

FOR
TAN SKIN
TONES

UVA/UVB BROAD SPECTRUM SPF 30
WATER RESISTANT 80 MINUTES
5FL OZ. (147mL)

PRINCIPAL DISPLAY PANEL - 147 mL Tube Label - Deep

GLO
WELL®

SPF30

TINTED
MINERAL
SUNSCREEN

ADAPTS TO SKIN TONE
WITH A BUILDABLE
GLOWING FINISH

FOR
DEEP SKIN
TONES

UVA/UVB BROAD SPECTRUM SPF 30
WATER RESISTANT 80 MINUTES
5FL OZ. (147mL)